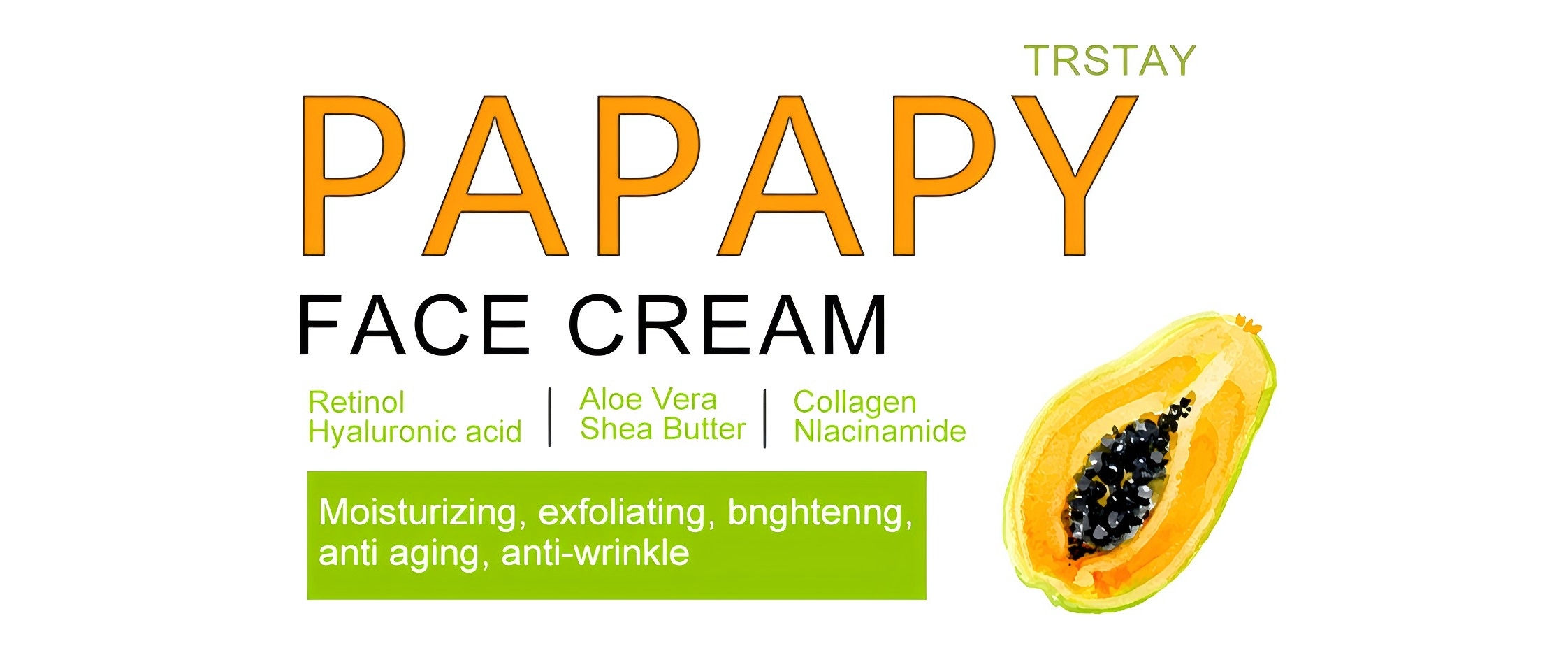 DRUG LABEL: Trstay Papapy Face Cream
NDC: 84682-615 | Form: CREAM
Manufacturer: Yiwu Yucheng E  Commerce Co Ltd
Category: otc | Type: HUMAN OTC DRUG LABEL
Date: 20241024

ACTIVE INGREDIENTS: NIACINAMIDE 5 g/100 g
INACTIVE INGREDIENTS: PALMITOYL PENTAPEPTIDE-4; PALMITOYL TRIPEPTIDE-1; SESAME OIL; CHLORPHENESIN; GLYCERIN

COMPONENTS

Salicylic acid 2%

INDICATIONS AND USAGE

Apply twice daly(moring and night as a man and once as a woman.Afer apicaion, proeed with an acive masage for 3-5 minutes unthe product is fuy absorbed

DOSAGE AND ADMINISTRATION

For external use only.

DO NOT USE

Discontinue use if any irritation or adverse reaction occurs

INACTIVE INGREDIENT

Acrylates copolymer, Ethyl acetate